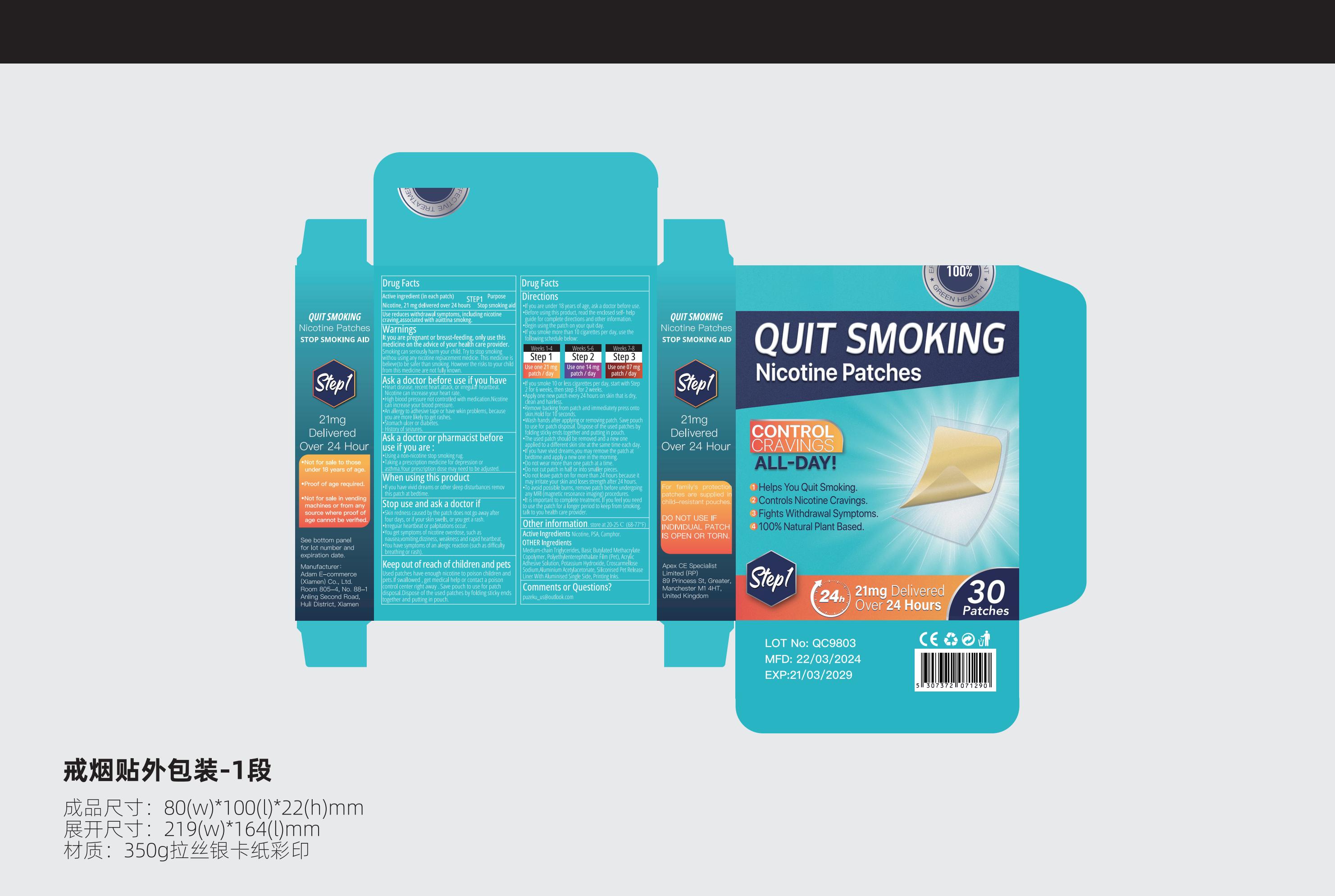 DRUG LABEL: Nicotine Patches
NDC: 84335-123 | Form: TABLET
Manufacturer: Adam E-commerce (Xiamen) Co., Ltd.
Category: otc | Type: HUMAN OTC DRUG LABEL
Date: 20240517

ACTIVE INGREDIENTS: PSATHYROTES RAMOSISSIMA WHOLE 36 g/100 g; N-(HYDROXYMETHYL)NICOTINAMIDE 36 g/100 g
INACTIVE INGREDIENTS: CROSCARMELLOSE SODIUM; POTASSIUM HYDROXIDE; ALUMINUM ACETYLACETONATE; CAMPHORIC ACID, (+)-; MEDIUM-CHAIN TRIGLYCERIDES

Warnings
It you are pregnant or breast-feeding,only use this medicine on the advice of yourhealth care provider.
Smoking can seriously harm your child.Try to stop smoking
withou using any nicotine repiacement medicie.This medicineisbelieve(to be safer than smoking.However therisksto your childfrom this medicine are not fuly known

INACTIVE INGREDIENT

Medium-chain Triglycerides, Basic Butylated MethacrylateCopolymer, Polyethylenterephthalate Film (Pet),

AcrylicAdhesive solution, Potassium Hydroxide, CroscarmelloseSodium,Aluminium Acetylacetonate, Siliconised Pet ReleaseLiner With Aluminised Single Side, Printing Inks

Keep out of reach of children and petsUsed patches have enough nicotine to poison children andpets.lf swallowed , get medical help or contact a poisoncontrol center right away . Save pouch to use for patchdisposal.Dispose of the used patches by folding sticky endstogether and putting in pouch

PURPOSE

1 Helps You Quit Smoking.2 Controls Nicotine Cravings,3 Fights Withdrawal Symptoms.4 100% Natural Plant Based.

INDICATIONS AND USAGE

Helps You Quit Smoking. Controls Nicotine Cravings. Fights Withdrawal Symptoms. 100% Natural Plant Based.

DOSAGE AND ADMINISTRATION

lf you smoke 10 or less cigarettes per day, start with Step2 for 6 weeks, then step 3 for 2 weeks.Apply one new patch every 24 hours on skin that is dry,clean and hairless.
Remove backing from patch and immediatety press ontoskin.Hold for 10 seconds.
Wash hands after applying or removing patch。 Save pouchto use for patch disposal. Dispose of the used patches byfolding sticky ends together and putting in pouch.The used patch should be removed and a new oneapplied to a different skin site at the same time each daylf you have vivid dreams,you may remove the patch atbedtime and apply a new one in the morning.Do not wear more than one patch at a time.Do not cut patch in half or into smaller pieces.Do not leave patch on for more than 24 hours because itmay irritate your skin and loses strength after 24 hours。

To avoid possible burns, remove patch before undergoingany MRl （magnetic resonance imaging) procedures.lt is important to complete treatment. lf you feel you needto use the patch for a longer period to keep from smokingtalk to you health care provider.

ACTIVE INGREDIENT

Nicotine, PsA, camphor

PACKAGE LABEL

1